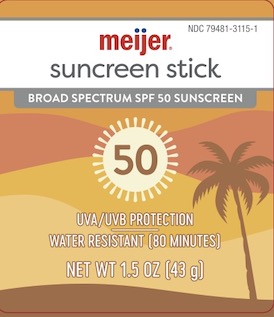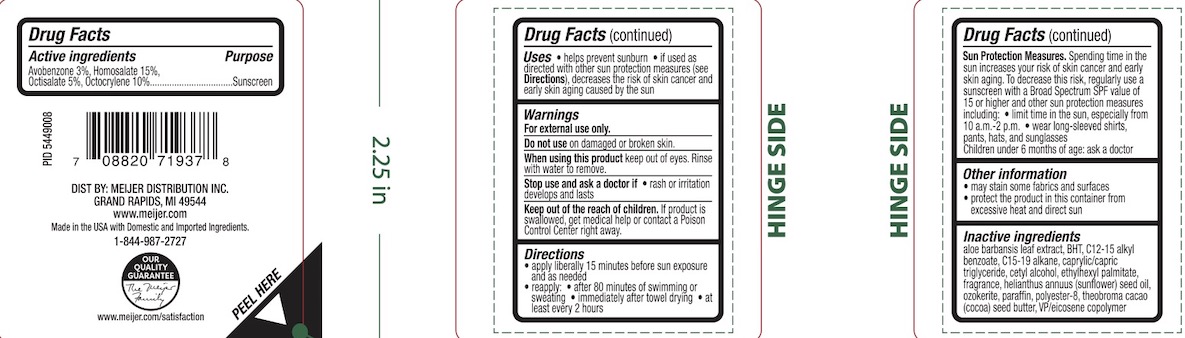 DRUG LABEL: Meijer SPF 50 Sunscreen
NDC: 79481-3115 | Form: STICK
Manufacturer: Meijer
Category: otc | Type: HUMAN OTC DRUG LABEL
Date: 20250127

ACTIVE INGREDIENTS: AVOBENZONE 3 g/100 g; OCTOCRYLENE 10 g/100 g; OCTISALATE 5 g/100 g; HOMOSALATE 15 g/100 g
INACTIVE INGREDIENTS: PARAFFIN; CAPRYLIC/CAPRIC TRIGLYCERIDE; COCOA BUTTER; C12-15 ALKYL BENZOATE; C15-19 ALKANE; HELIANTHUS ANNUUS (SUNFLOWER) SEED OIL; EICOSYL POVIDONE; CERESIN; CETYL ALCOHOL; BHT; ETHYLHEXYL PALMITATE; POLYESTER-8 (1400 MW, CYANODIPHENYLPROPENOYL CAPPED)

Meijer SPF 50 Sunscreen Stick

ACTIVE INGREDIENT

Avobenzone 3%, Homosalate 15%, Octisalate 5%, Octocrylene 10%

PURPOSE

Sunscreen

INDICATIONS AND USAGE

Helps prevent sunburn.

If used as directed with other sun protection measures (see Directions), decreases the risk of skin cancer and early skin aging caused by the sun.

WARNINGS

For external use only.

Do not use on damaged or broken skin.

When using this product avoid contact with eyes. Rinse with water to remove.

Stop use and ask a doctor if rash or irritation develops and lasts.

KEEP OUT OF REACH OF CHILDREN

If product is swallowed, get medical help or contact a Poison Control Center right away.

DOSAGE AND ADMINISTRATION

Apply liberally 15 minutes before sun exposure. Reapply: after 80 minutes of swimming or sweating, immediately after towel drying, at least every 2 hours.

Sun Protection Measures. Spending time in the sun increases your risk of skin cancer and early skin aging. To decrease this risk, regularly use a sunscreen with a Broad Spectrum SPF value of 15 or higher and other sun protection measures including: limit time in the sun, especially from 10 a.m. - 2 p.m., wear long-sleeved shirts, pants, hats, and sunglasses, children under 6 months of age: ask a doctor.

INACTIVE INGREDIENT

Aloe barbadensis leaf extract, BHT, C12-15 alkyl benzoate, C15-19 alkane, caprylic/capric triglyceride, cetyl alcohol, ethylhexyl palmitate, fragrance, helianthus annuus (sunflower) seed oil, ozokerite, paraffin, polyester-8, theobroma cacao (cocoa) seed butter, VP/eicosene copolymer.